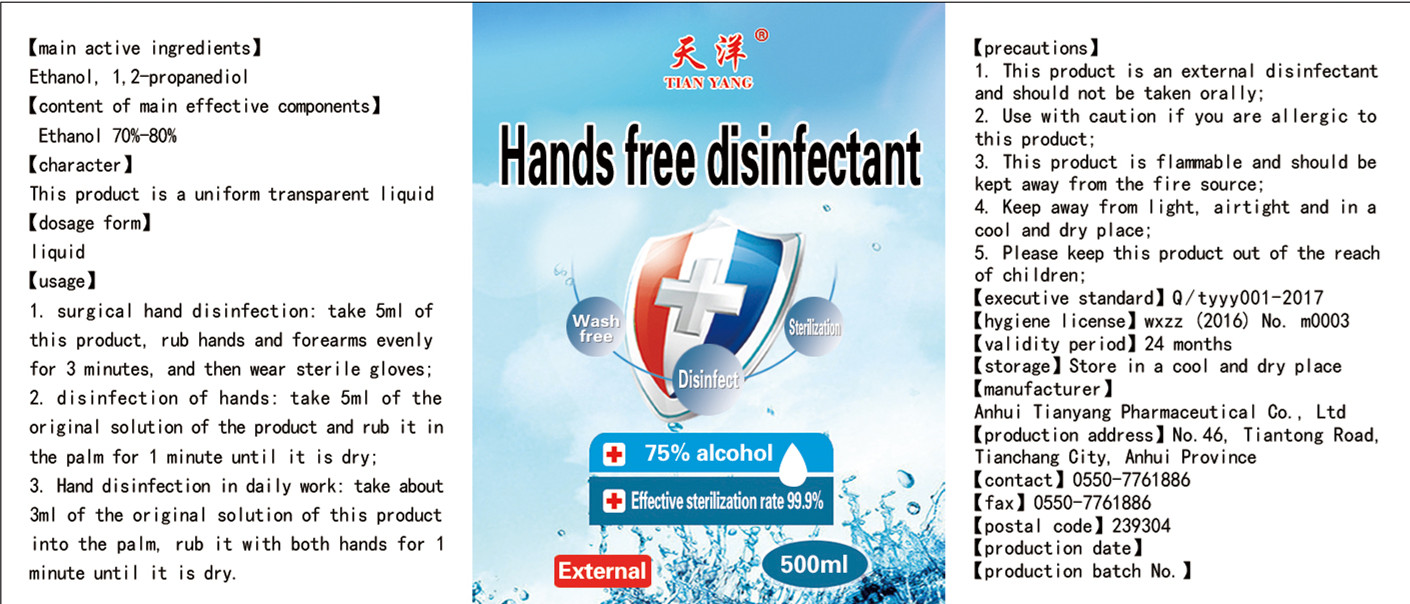 DRUG LABEL: TIANYANG HandSanitizer
NDC: 52983-001 | Form: LIQUID
Manufacturer: Anhui Tianyang Pharmaceutical Co., Ltd.
Category: otc | Type: HUMAN OTC DRUG LABEL
Date: 20200429

ACTIVE INGREDIENTS: ALCOHOL 375 mL/500 mL
INACTIVE INGREDIENTS: PROPYLENE GLYCOL

DOSAGE AND ADMINISTRATION

Keep away from light, airtight and in a cool and dry place.

INACTIVE INGREDIENT

1,2 propylene glycol

INDICATIONS AND USAGE

1. surgical hand disinfection: take 5ml of this product， rub hands and for earms evenly for 3 minutes, and then wear sterile gloves;
2. disinfection of hands: take 5m| of the original solution of the product and rub it in the palm for 1 minute until it is dry;
3. Hand disinfection in daily work: take about 3ml of the original solution of this product into the palm，rub it with both hands for 1
minute until it is dry.

ACTIVE INGREDIENT

Alcohol

keep out of reach of children

PURPOSE

Disinfection
Sterilization
No Rinseing

WARNINGS

1. This product is an external dis infectant and should not be taken orally;
2. Use with caution if you are allergic to this product;
3. This product is flammable and should be kept away from the fire source;
4. Keep away from light, airtight and in a cool and dry pl ace;
5. Please keep this product out of the reach of chi Idren;